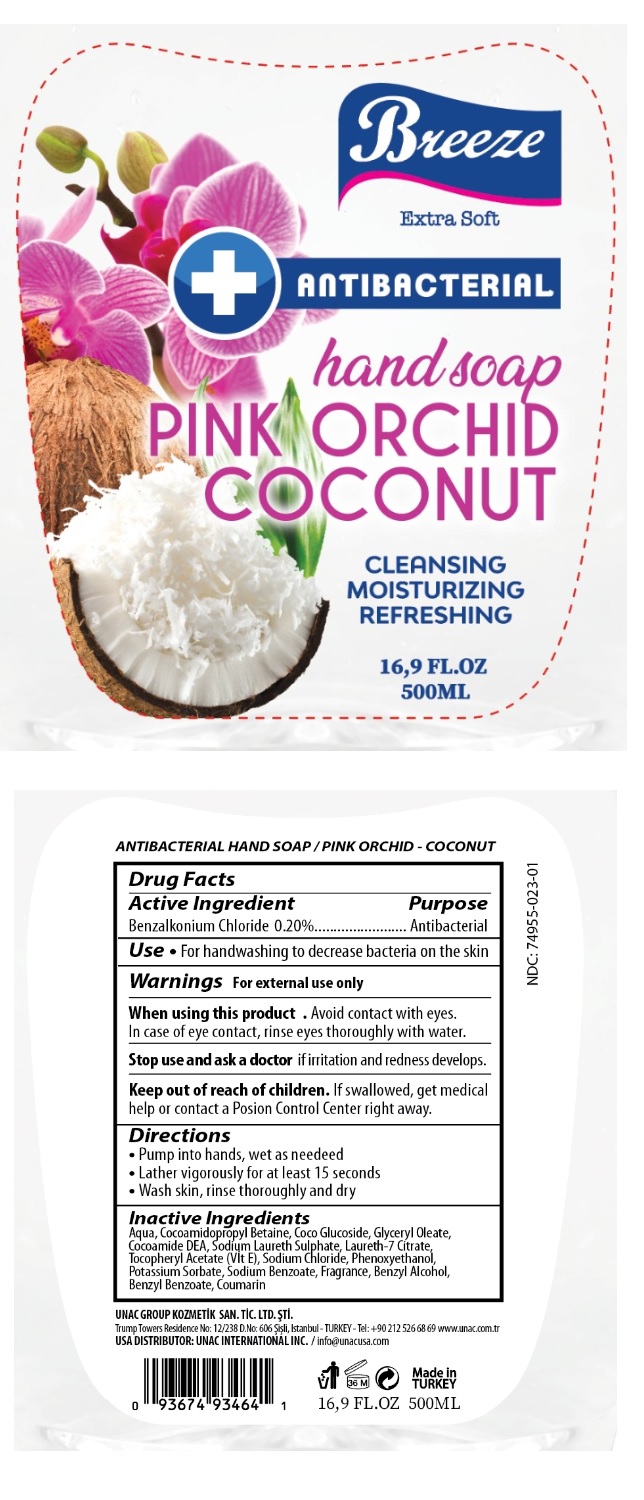 DRUG LABEL: Breeze ANTIBACTERIAL handsoap PINK ORCHID COCONUT
NDC: 74955-023 | Form: LIQUID
Manufacturer: COSMOLIVE KOZMETIK SANAYI VE TICARET ANONIM SIRKETI
Category: otc | Type: HUMAN OTC DRUG LABEL
Date: 20200813

ACTIVE INGREDIENTS: BENZALKONIUM CHLORIDE 0.20 g/100 mL
INACTIVE INGREDIENTS: WATER; COCAMIDOPROPYL BETAINE; COCO GLUCOSIDE; GLYCERYL OLEATE; COCO DIETHANOLAMIDE; SODIUM LAURETH-3 SULFATE; LAURETH-7; .ALPHA.-TOCOPHEROL ACETATE; SODIUM CHLORIDE; PHENOXYETHANOL; POTASSIUM SORBATE; SODIUM BENZOATE; BENZYL ALCOHOL; BENZYL BENZOATE; COUMARIN

Breeze ANTIBACTERIAL handsoap PINK ORCHID COCONUT

Active Ingredient

Benzalkonium Chloride 0.20%

Purpose

Antibacterial

INDICATIONS AND USAGE

Use • For handwashing to decrease bacteria on the skin

Warnings For external use only

When using this product • Avoid contact with eyes. In case of eye contact, rinse eyes thoroughly with water.

Stop use and ask a doctor if irritation and redness develop.

Keep out of reach of children. If swallowed, get medical help or contact a Poison Control Center right away.

Directions

• Pump into hands, wet as needed

• Lather vigorously for at least 15 seconds

• Wash skin, rinse thoroughly and dry

Inactive Ingredients

Aqua, Cocoamidopropyl Betaine, Coco Glucoside, Glyceryl Oleate, Cocoamide DEA, Sodium Laureth Sulphate, Laureth-7 Citrate, Tocopheryl Acetate (Vit E), Sodium Chloride, Phenoxyethanol, Potassium Sorbate, Sodium Benzoate, Parfume, Benzyl Alcohol, Benzyl Benzoate, Coumarin

Extra Soft

CLEANSING

MOISTURIZING

REFRESHING

UNAC GROUP KOZMETIK SAN. TIC LTD. STI

Trump Towers Residence No: 12/238 D. No:606 Sisli, Istanbul- TURKEY - Tel: +90 212 526 68 69 www.unac.com.tr

USA DISTRIBUTOR: UNAC INTERNATIONAL INC. / info@unacusa.com

Made in TURKEY